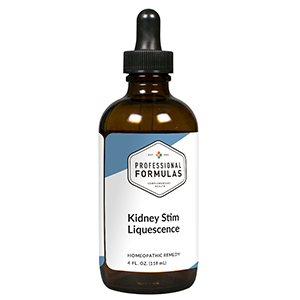 DRUG LABEL: Kidney Stim Liquescence
NDC: 63083-3013 | Form: LIQUID
Manufacturer: Professional Complementary Health Formulas
Category: homeopathic | Type: HUMAN OTC DRUG LABEL
Date: 20190815

ACTIVE INGREDIENTS: JUNIPERUS COMMUNIS VAR. SAXATILIS WHOLE 2 [hp_X]/118 mL; ARCTOSTAPHYLOS TOMENTOSA WHOLE 2 [hp_X]/118 mL; EQUISETUM HYEMALE WHOLE 3 [hp_X]/118 mL; TARAXACUM OFFICINALE 3 [hp_X]/118 mL; URTICA DIOICA WHOLE 3 [hp_X]/118 mL; BERBERIS VULGARIS ROOT BARK 6 [hp_X]/118 mL; SUS SCROFA URINARY BLADDER 6 [hp_X]/118 mL; LYTTA VESICATORIA 6 [hp_X]/118 mL; EUTROCHIUM PURPUREUM ROOT 6 [hp_X]/118 mL; BEEF KIDNEY 6 [hp_X]/118 mL; CALCIUM SULFIDE 8 [hp_X]/118 mL; NITRIC ACID 8 [hp_X]/118 mL; BENZOIC ACID 12 [hp_X]/118 mL; BOS TAURUS SPLEEN 12 [hp_X]/118 mL
INACTIVE INGREDIENTS: ALCOHOL; WATER

T13

ACTIVE INGREDIENTS

Juniperus communis 2X
Uva-ursi 2X, 3X
Equisetum hyemale 3X
Taraxacum officinale 3X
Urtica dioica 3X
Berberis vulgaris 6X
Bladder 6X
Cantharis 6X
Eupatorium purpureum 6X
Kidney 6X
Hepar sulphuris calcareum 8X
Nitricum acidum 8X
Benzoicum acidum 12X
Ren bovis 12X

QUESTIONS

Professional Formulas

PO Box 2034 Lake Oswego, OR 97035

INDICATIONS

For the temporary relief of minor nausea, changes in appetite, fatigue, disturbed sleep, muscle twitches, or cramps.*

PURPOSE

*Claims based on traditional homeopathic practice, not accepted medical evidence. Not FDA evaluated.

WARNINGS

Severe or persistent symptoms may be serious. Consult a doctor promptly. Keep out of the reach of children. In case of overdose, get medical help or contact a poison control center right away. If pregnant or breastfeeding, ask a healthcare professional before use.

Keep out of the reach of children.

PREGNANCY OR BREAST FEEDING

If pregnant or breastfeeding, ask a healthcare professional before use.

DIRECTIONS

Place drops under tongue 30 minutes before/after meals. Adults and children 12 years and over: Take one full dropper up to 2 times per day. Consult a physician for use in children under 12 years of age.

OTHER INFORMATION

Tamper resistant. If seal is broken, do not use. After opening, close container tightly and store at room temperature away from heat.

INACTIVE INGREDIENTS

20% ethanol, purified water.

LABEL

Est 1985

Professional Formulas

Complementary Health

Kidney Stim Liquescence

Homeopathic Remedy

4 FL. OZ. (118 mL)